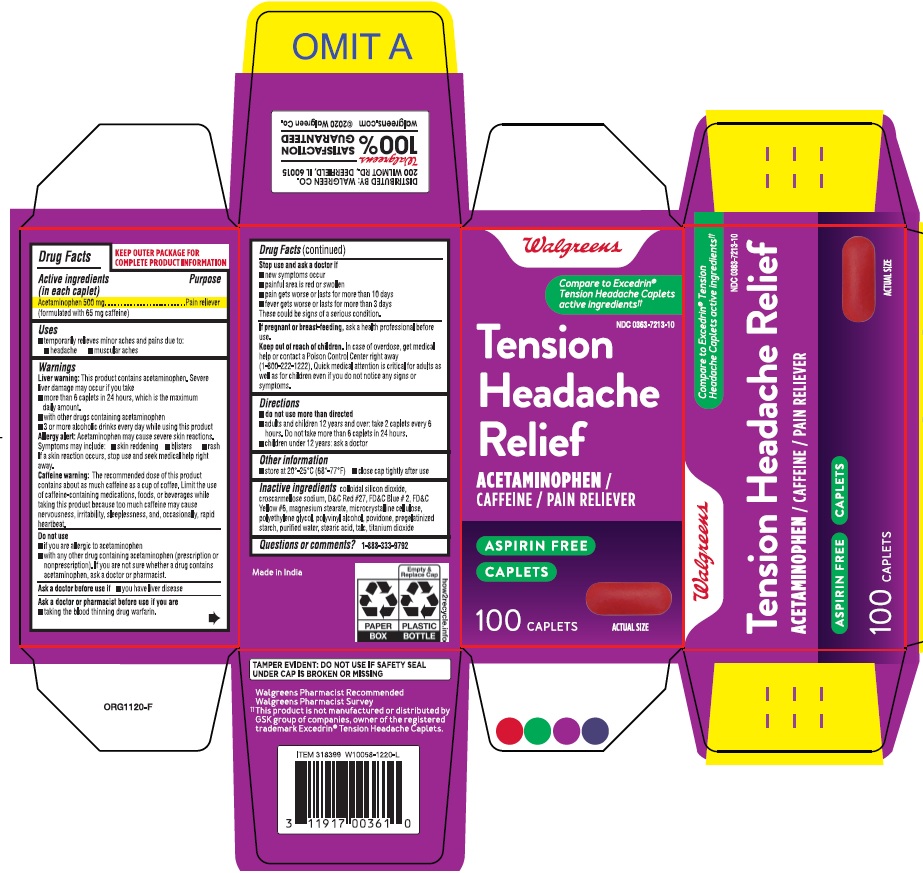 DRUG LABEL: TENSION HEADACHE RELIEF
NDC: 0363-7213 | Form: TABLET
Manufacturer: WALGREENS
Category: otc | Type: HUMAN OTC DRUG LABEL
Date: 20260116

ACTIVE INGREDIENTS: ACETAMINOPHEN 500 mg/1 1; CAFFEINE 65 mg/1 1
INACTIVE INGREDIENTS: SILICON DIOXIDE; CROSCARMELLOSE SODIUM; D&C RED NO. 27; FD&C BLUE NO. 2; FD&C YELLOW NO. 6; MAGNESIUM STEARATE; MICROCRYSTALLINE CELLULOSE; POLYETHYLENE GLYCOL, UNSPECIFIED; POLYVINYL ALCOHOL, UNSPECIFIED; POVIDONE K30; STARCH, PREGELATINIZED CORN; WATER; STEARIC ACID; TALC; TITANIUM DIOXIDE

TENSION HEADACHE RELIEF

Drug Facts

PURPOSE

Active ingredients (in each caplet) | Purposes
Acetaminophen 500 mg | Pain reliever
Caffeine 65 mg | Pain reliever aid

Uses

- temporarily relieves minor aches and pains due to:
- headache
- muscular aches

Warnings

Liver Warning: This product contains acataminophen. Severe liver damage may occure if you take.

- more than 6 caplets in 24 hours, whihc is the maximum daily amount.
- with other drugs containing acetaminophen
- 3 or more alcoholic drinks every day while using this product

Allergy alert: Acetaminophen may cause severe skin reactions.

Symptoms may include:

- skin reddening
- blisters
- rash

If a skin reaction occurs, stop use and seek medical help right away.

Caffeine warning: The recommended dose of this product contains about as much caffeine as a cup of coffee. Limit the use of caffeine-containing medications, foods, beverages while taking this product because too much caffeine may cause nervousness, irritability, sleeplessness, and, occasionally, rapid heartbeat.

Do not use

- if you are allergic to acetaminophen
- with any other drug containing acetaminophen (prescription or nonprescription). If you are not sure whether a drug contains acetaminophen, ask a doctor or pharmacist.

Ask a doctor before use if you have

- liver disease

Ask a doctor or pharmacist before use if you are

- taking the blood thinning drug warfarin

Stop use and ask a doctor if

- any new symptoms occur
- painful area is red or swollen
- pain gets worse or lasts more than 10 days
- fever gets worse or lasts for more than 3 days

These could be signs of a serious condition

If pregnant or breast feeding,

ask a health professional before use.

Keep Out of Reach of Children

In case of overdose, get medical help or contact a Poison Control Center right away. Quick medical attention is critical for adults as well as for children even if you do not notice any signs or symptoms. 1-800-222-1222

Directions

- do not use more than directed
- adults and children 12 years and over; take 2 caplets every 6 hours; not more than 6 caplets in 24 hours
- children under 12 years: ask a doctor

Other information

- store at 20°-25°C (68°-77°F)
- close cap tightly after use
- read all product information before using. Keep this box for important information.

Inactive ingredients

colloidal silicon dioxide, croscarmellose sodium, D&C Red#27, FD&C Blue#2, FD&C Yellow#6, magnesium stearate, microcrystalline cellulose, polyethylene glycol, polyvinyl alcohol, povidone, pregelatinized starch, purified water, stearic acid, talc, titanium dioxide

Questions or comments?

1-888-333-9792

PRINCIPAL DISPLAY PANEL

Tension Headache Relief

• Acetaminophen & Caffeine

Pain Reliever/ Pain reliever aid

Actual Size